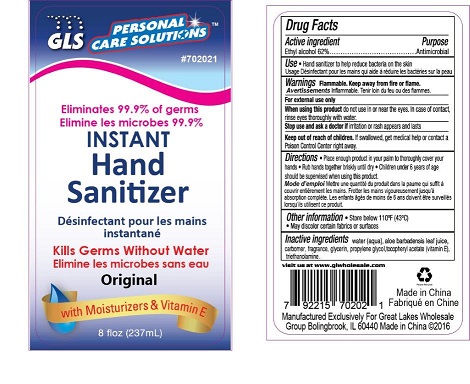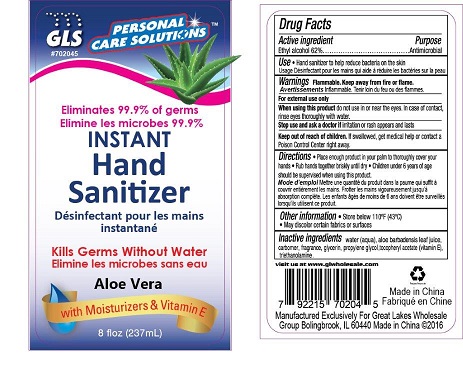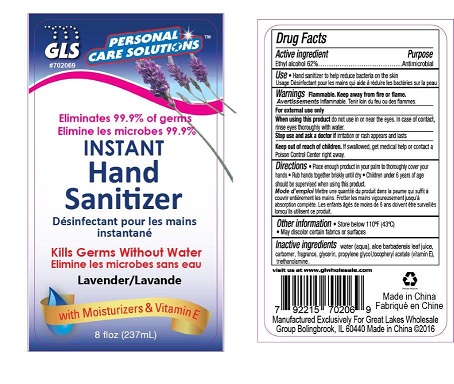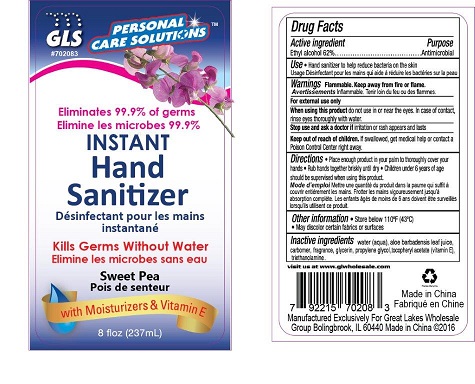 DRUG LABEL: skin protectant
NDC: 64092-321 | Form: LIQUID
Manufacturer: Great lakes Wholesale, Marketing, and Sales, Inc.
Category: otc | Type: HUMAN OTC DRUG LABEL
Date: 20160830

ACTIVE INGREDIENTS: ALCOHOL 146.94 mL/237 mL
INACTIVE INGREDIENTS: WATER

DESCRIPTION

GLS PERSONAL CARE SOLUTIONS

Instant Hand Sanitizer

Eliminates 99.9% of germs

Kills Germs Without Water

with Moisturizers & Vitamin E

8 fl. oz (237mL)

Original, Aloe Vera, Lavender, Sweet Pea

Active Ingredient Purpose

Ethyl alcohol 62%.................................................Antimicrobial

PURPOSE

Kill germs without water

INDICATIONS AND USAGE

To help reduce bacteria on the skin

WARNINGS

Flammable. Keep away from fire or flame.

For external use only

When using this product do not use in or near the eyes. In case of contact, rinse eyes throughly with water.

Stop use and ask a doctor if irritation or rash appears and lasts.

KEEP OUT OF REACH OF CHILDREN

If swallowed, get medical help or contact a Poison control Center right away.

INSTRUCTIONS FOR USE

- Place enough product in your palm to thoroughly cover your hands
- Rub hands together briskly until dry
- Children under 6 years of age should be supervised when using this product. .

DOSAGE AND ADMINISTRATION

Instant Hand Sanitizer

62% Ethyl alcohol

STORAGE AND HANDLING

- Store below 110°F(43°C)
- May discolor certain fabrics or surfaces.

INACTIVE INGREDIENT

water (aqua), aloe barbadensis leaf juice, carbomer, fragrance, glyerin, propylene glycol, tocopheryl acetate (vitamin E), triethanolamine.